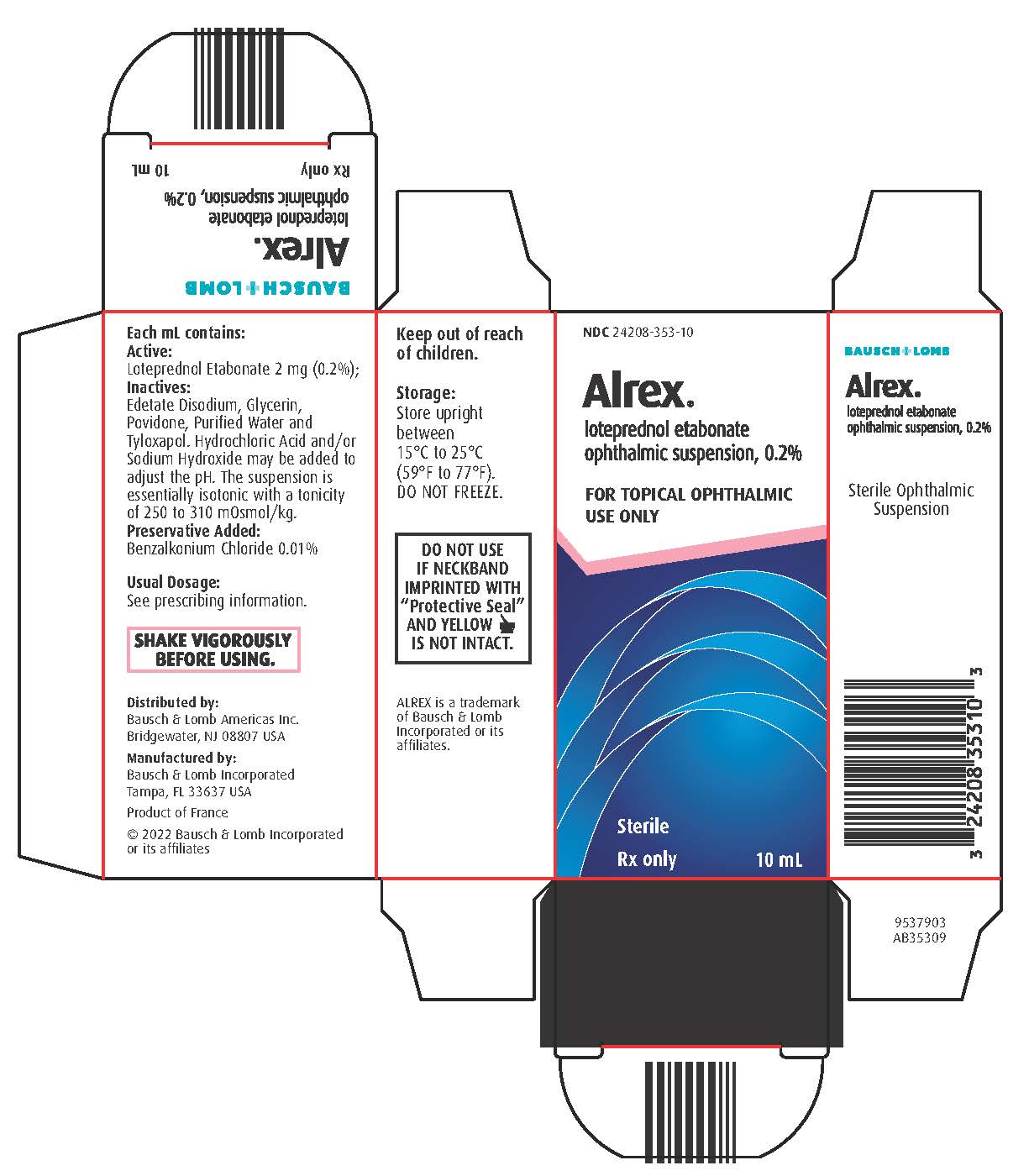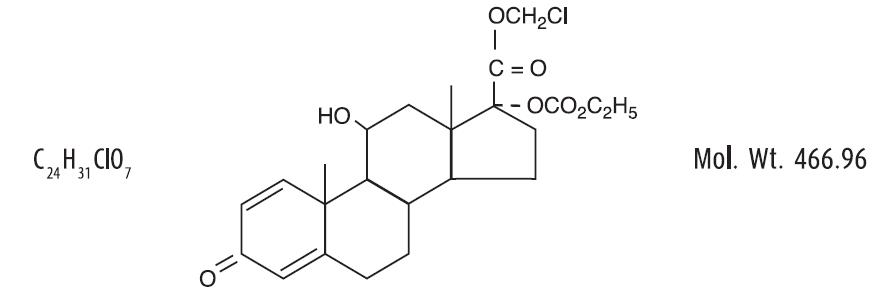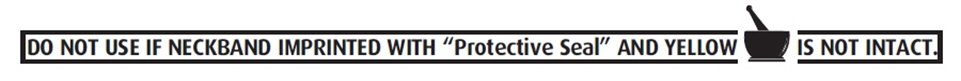 DRUG LABEL: Alrex
NDC: 24208-353 | Form: SUSPENSION/ DROPS
Manufacturer: Bausch & Lomb Incorporated
Category: prescription | Type: HUMAN PRESCRIPTION DRUG LABEL
Date: 20220331

ACTIVE INGREDIENTS: LOTEPREDNOL ETABONATE 2 mg/1 mL
INACTIVE INGREDIENTS: BENZALKONIUM CHLORIDE 0.1 mg/1 mL; EDETATE DISODIUM; GLYCERIN; WATER; TYLOXAPOL; HYDROCHLORIC ACID; SODIUM HYDROXIDE; POVIDONE, UNSPECIFIED

Alrex® (loteprednol etabonate
ophthalmic suspension, 0.2%)
STERILE OPHTHALMIC SUSPENSION

DESCRIPTION

ALREX® (loteprednol etabonate ophthalmic suspension, 0.2%) contains a sterile, topical anti-inflammatory corticosteroid for ophthalmic use. Loteprednol etabonate is a white to off-white powder.

Loteprednol etabonate is represented by the following structural formula:

Chemical Name:
chloromethyl 17α-[(ethoxycarbonyl)oxy]-11β-hydroxy-3-oxoandrosta-1,4-diene-17β-carboxylate

Each mL contains:

ACTIVE: Loteprednol Etabonate 2 mg (0.2%);

INACTIVES: Edetate Disodium, Glycerin, Povidone, Purified Water and Tyloxapol. Hydrochloric Acid and/or Sodium Hydroxide may be added to adjust the pH. The suspension is essentially isotonic with a tonicity of 250 to 310 mOsmol/kg.

PRESERVATIVE ADDED: Benzalkonium Chloride 0.01%.

CLINICAL PHARMACOLOGY

Corticosteroids inhibit the inflammatory response to a variety of inciting agents and probably delay or slow healing. They inhibit the edema, fibrin deposition, capillary dilation, leukocyte migration, capillary proliferation, fibroblast proliferation, deposition of collagen, and scar formation associated with inflammation. There is no generally accepted explanation for the mechanism of action of ocular corticosteroids. However, corticosteroids are thought to act by the induction of phospholipase A2 inhibitory proteins, collectively called lipocortins. It is postulated that these proteins control the biosynthesis of potent mediators of inflammation such as prostaglandins and leukotrienes by inhibiting the release of their common precursor arachidonic acid. Arachidonic acid is released from membrane phospholipids by phospholipase A2. Corticosteroids are capable of producing a rise in intraocular pressure.

Loteprednol etabonate is structurally similar to other corticosteroids. However, the number 20 position ketone group is absent. It is highly lipid soluble which enhances its penetration into cells. Loteprednol etabonate is synthesized through structural modifications of prednisolone-related compounds so that it will undergo a predictable transformation to an inactive metabolite. Based upon in vivo and in vitro preclinical metabolism studies, loteprednol etabonate undergoes extensive metabolism to inactive carboxylic acid metabolites.

Results from a bioavailability study in normal volunteers established that plasma levels of loteprednol etabonate and Δ^1 cortienic acid etabonate (PJ 91), its primary, inactive metabolite, were below the limit of quantitation (1 ng/mL) at all sampling times. The results were obtained following the ocular administration of one drop in each eye of 0.5% loteprednol etabonate 8 times daily for 2 days or 4 times daily for 42 days. This study suggests that limited (<1 ng/mL) systemic absorption occurs with ALREX.

Clinical Studies:

In two double-masked, placebo-controlled six-week environmental studies of 268 patients with seasonal allergic conjunctivitis, ALREX, when dosed four times per day was superior to placebo in the treatment of the signs and symptoms of seasonal allergic conjunctivitis. ALREX provided reduction in bulbar conjunctival injection and itching, beginning approximately 2 hours after instillation of the first dose and throughout the first 14 days of treatment.

INDICATIONS AND USAGE

ALREX ophthalmic suspension is indicated for the temporary relief of the signs and symptoms of seasonal allergic conjunctivitis.

CONTRAINDICATIONS

ALREX, as with other ophthalmic corticosteroids, is contraindicated in most viral diseases of the cornea and conjunctiva including epithelial herpes simplex keratitis (dendritic keratitis), vaccinia, and varicella, and also in mycobacterial infection of the eye and fungal diseases of ocular structures. ALREX is also contraindicated in individuals with known or suspected hypersensitivity to any of the ingredients of this preparation and to other corticosteroids.

WARNINGS

Prolonged use of corticosteroids may result in glaucoma with damage to the optic nerve, defects in visual acuity and fields of vision, and in posterior subcapsular cataract formation. Steroids should be used with caution in the presence of glaucoma.

Prolonged use of corticosteroids may suppress the host response and thus increase the hazard of secondary ocular infections. In those diseases causing thinning of the cornea or sclera, perforations have been known to occur with the use of topical steroids. In acute purulent conditions of the eye, steroids may mask infection or enhance existing infection.

Use of ocular steroids may prolong the course and may exacerbate the severity of many viral infections of the eye (including herpes simplex). Employment of a corticosteroid medication in the treatment of patients with a history of herpes simplex requires great caution.

PRECAUTIONS

General:

For ophthalmic use only. The initial prescription and renewal of the medication order beyond 14 days should be made by a physician only after examination of the patient with the aid of magnification, such as slit lamp biomicroscopy and, where appropriate, fluorescein staining.

If signs and symptoms fail to improve after two days, the patient should be re-evaluated.

If this product is used for 10 days or longer, intraocular pressure should be monitored.

Fungal infections of the cornea are particularly prone to develop coincidentally with long-term local steroid application. Fungus invasion must be considered in any persistent corneal ulceration where a steroid has been used or is in use. Fungal cultures should be taken when appropriate.

Information for Patients:

This product is sterile when packaged. Patients should be advised not to allow the dropper tip to touch any surface, as this may contaminate the suspension. If redness or itching becomes aggravated, the patient should be advised to consult a physician.

Patients should be advised not to wear a contact lens if their eye is red. ALREX should not be used to treat contact lens related irritation. The preservative in ALREX, benzalkonium chloride, may be absorbed by soft contact lenses. Patients who wear soft contact lenses and whose eyes are not red, should be instructed to wait at least ten minutes after instilling ALREX before they insert their contact lenses.

Carcinogenesis, Mutagenesis, Impairment of Fertility:

Long-term animal studies have not been conducted to evaluate the carcinogenic potential of loteprednol etabonate. Loteprednol etabonate was not genotoxic in vitro in the Ames test, the mouse lymphoma tk assay, or in a chromosome aberration test in human lymphocytes, or in vivo in the single dose mouse micronucleus assay. Treatment of male and female rats with up to 50 mg/kg/day and 25 mg/kg/day of loteprednol etabonate, respectively, (1,500 and 750 times the maximum clinical dose, respectively) prior to and during mating did not impair fertility in either gender.

Pregnancy:

Teratogenic effects:

Loteprednol etabonate has been shown to be embryotoxic (delayed ossification) and teratogenic (increased incidence of meningocele, abnormal left common carotid artery, and limb flexures) when administered orally to rabbits during organogenesis at a dose of 3 mg/kg/day (85 times the maximum daily clinical dose), a dose which caused no maternal toxicity. The no-observed-effect-level (NOEL) for these effects was 0.5 mg/kg/day (15 times the maximum daily clinical dose). Oral treatment of rats during organogenesis resulted in teratogenicity (absent innominate artery at ≥5 mg/kg/day doses, and cleft palate and umbilical hernia at ≥50 mg/kg/day) and embryotoxicity (increased postimplantation losses at 100 mg/kg/day and decreased fetal body weight and skeletal ossification with ≥50 mg/kg/day). Treatment of rats with 0.5 mg/kg/day (15 times the maximum clinical dose) during organogenesis did not result in any reproductive toxicity. Loteprednol etabonate was maternally toxic (significantly reduced body weight gain during treatment) when administered to pregnant rats during organogenesis at doses of ≥5 mg/kg/day.

Oral exposure of female rats to 50 mg/kg/day of loteprednol etabonate from the start of the fetal period through the end of lactation, a maternally toxic treatment regimen (significantly decreased body weight gain), gave rise to decreased growth and survival, and retarded development in the offspring during lactation; the NOEL for these effects was 5 mg/kg/day. Loteprednol etabonate had no effect on the duration of gestation or parturition when administered orally to pregnant rats at doses up to 50 mg/kg/day during the fetal period.

There are no adequate and well controlled studies in pregnant women. ALREX ophthalmic suspension should be used during pregnancy only if the potential benefit justifies the potential risk to the fetus.

Nursing Mothers:

It is not known whether topical ophthalmic administration of corticosteroids could result in sufficient systemic absorption to produce detectable quantities in human milk. Systemic steroids appear in human milk and could suppress growth, interfere with endogenous corticosteroid production, or cause other untoward effects. Caution should be exercised when ALREX is administered to a nursing woman.

Pediatric Use:

Safety and effectiveness in pediatric patients have not been established.

ADVERSE REACTIONS

Reactions associated with ophthalmic steroids include elevated intraocular pressure, which may be associated with optic nerve damage, visual acuity and field defects, posterior subcapsular cataract formation, secondary ocular infection from pathogens including herpes simplex, and perforation of the globe where there is thinning of the cornea or sclera.

Ocular adverse reactions occurring in 5-15% of patients treated with loteprednol etabonate ophthalmic suspension (0.2-0.5%) in clinical studies included abnormal vision/blurring, burning on instillation, chemosis, discharge, dry eyes, epiphora, foreign body sensation, itching, injection, and photophobia. Other ocular adverse reactions occurring in less than 5% of patients include conjunctivitis, corneal abnormalities, eyelid erythema, keratoconjunctivitis, ocular irritation/pain/discomfort, papillae, and uveitis. Some of these events were similar to the underlying ocular disease being studied.

Non-ocular adverse reactions occurred in less than 15% of patients. These include headache, rhinitis and pharyngitis.

In a summation of controlled, randomized studies of individuals treated for 28 days or longer with loteprednol etabonate, the incidence of significant elevation of intraocular pressure (≥10 mm Hg) was 2% (15/901) among patients receiving loteprednol etabonate, 7% (11/164) among patients receiving 1% prednisolone acetate and 0.5% (3/583) among patients receiving placebo. Among the smaller group of patients who were studied with ALREX, the incidence of clinically significant increases in IOP (≥10 mm Hg) was 1% (1/133) with ALREX and 1% (1/135) with placebo.

To report SUSPECTED ADVERSE REACTIONS, contact Bausch & Lomb Incorporated at 1-800-553-5340 or FDA at 1-800-FDA-1088 or www.fda.gov/medwatch.

DOSAGE AND ADMINISTRATION

SHAKE VIGOROUSLY BEFORE USING.
One drop instilled into the affected eye(s) four times daily.

HOW SUPPLIED

ALREX® (loteprednol etabonate ophthalmic suspension, 0.2%) is supplied in a plastic bottle with a controlled drop tip in the following sizes:

NDC 24208-353-05 5 mL in a 7.5 mL bottle
NDC 24208-353-10 10 mL in a 10 mL bottle

Storage:

Store upright between 15°C to 25°C (59°F to 77°F). DO NOT FREEZE.

Distributed by:

Bausch & Lomb Americas Inc.

Bridgewater, NJ 08807 USA

Manufactured by:

Bausch & Lomb Incorporated

Tampa, FL 33637 USA

ALREX is a trademark of Bausch & Lomb Incorporated or its affiliates.

© 2022 Bausch & Lomb Incorporated or its affiliates

Revised: 03/2022

9007907 (Folded)

9005507 (Flat)

Principal Display Panel

9537903
AB35309

NDC 24208-353-10

Alrex®
loteprednol etabonate
ophthalmic suspension, 0.2%
FOR OPHTHALMIC USE ONLY
Sterile

Rx only
10 mL